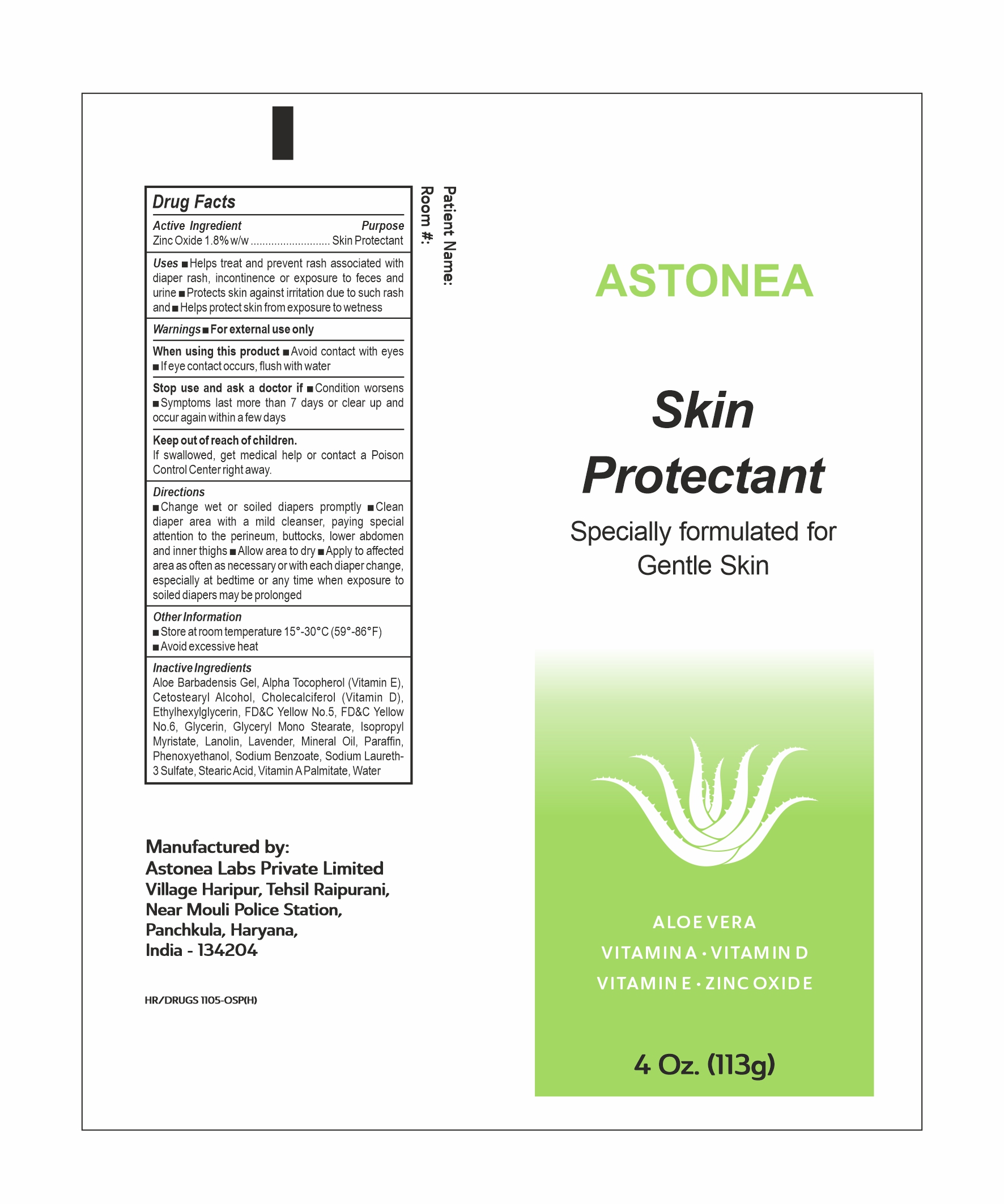 DRUG LABEL: Astonea Skin Protectant
NDC: 77338-050 | Form: OINTMENT
Manufacturer: ASTONEA LABS PRIVATE LIMITED
Category: otc | Type: HUMAN OTC DRUG LABEL
Date: 20240625

ACTIVE INGREDIENTS: ZINC OXIDE 18 mg/1 g
INACTIVE INGREDIENTS: ETHYLHEXYLGLYCERIN; VITAMIN A PALMITATE; WATER; GLYCERYL MONOSTEARATE; SODIUM LAURETH-3 SULFATE; FD&C YELLOW NO. 6; ISOPROPYL MYRISTATE; LAVENDER OIL; SODIUM BENZOATE; FD&C YELLOW NO. 5; STEARIC ACID; ALOE VERA LEAF; ALPHA-TOCOPHEROL; CETOSTEARYL ALCOHOL; CHOLECALCIFEROL; GLYCERIN; LANOLIN; MINERAL OIL; PARAFFIN; PHENOXYETHANOL

Astonea skin protectant 1.8% ZNO

Active ingredient

Zinc Oxide (1.8% w/w)

Purpose

Skin Protectant

Uses:

- Helps treat and prevent diaper rash, incontinence or exposure to feces and urine
- Protects Skin against irritation due to such rash and
- Helps protect skin from exposure to wetness

Warnings:

For external use only

When using this product

- Avoid contact with eyes
- If eye contact occurs, flush with water

Stop use and ask a doctor if:

- Condition worsens or does not improve within seven days

Keep out of reach of children

- If swallowed, get medical help or contact a Poison Control Center right away

Directions:

- Change wet or solied diapers promptly
- Clean diaper area with a mild cleanser, paying special attention to the perinium, buttocks, lower abdomen and inner thighs
- Allow to dry
- Apply to affected area as often as necessary or with each diaper change, especially at bedtime or any time when exposure to soiled diapers may be prolonged

Other information:

- Store at room temperature 15º - 30ºC (59º - 86ºF)
- Avoid excessive heat

Inactive ingredients:

Aloe Barbadensis Gel, Alpha-Tocopherol(Vitamin E), Cetostearyl Alcohol, Cholecalciferol (Vitamin D), Ethylhexylglycerine, FD&C Yellow No. 5, FD&C Yellow No. 6, Glycerin, Glyceryl Monostearate, Isopropyl Myristate, Lanolin, Lavender, Mineral Oil, Paraffin, Phenoxyethanol, Sodium Benzoate, Sodium Laureth-3 Sulfate, stearic acid, Vitamin A Palmitate, Water.